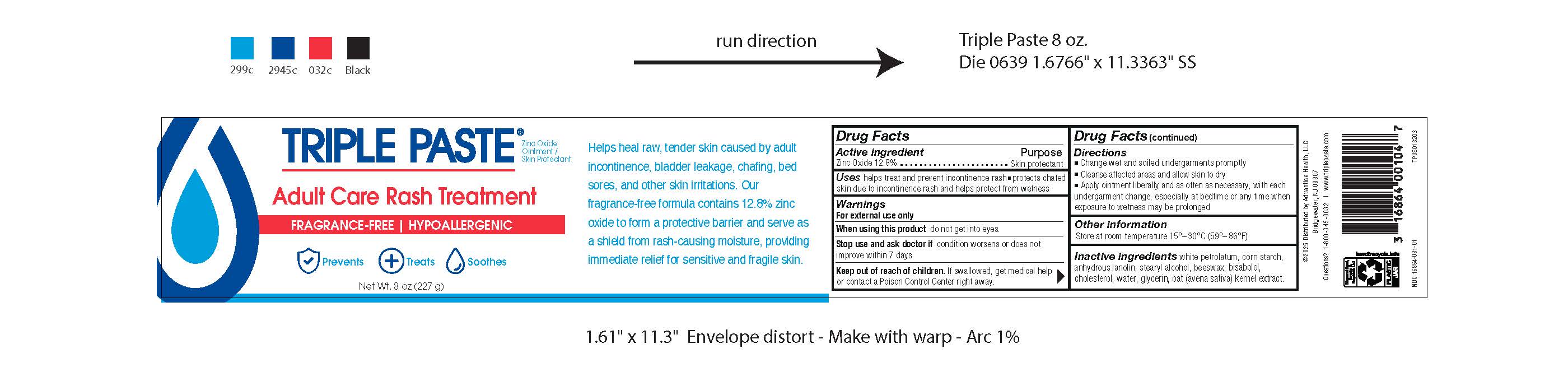 DRUG LABEL: TriplePaste Adult Care Rash Treatment
NDC: 16864-031 | Form: PASTE
Manufacturer: Advantice Health, LLC
Category: otc | Type: HUMAN OTC DRUG LABEL
Date: 20250130

ACTIVE INGREDIENTS: ZINC OXIDE 12.8 g/100 g
INACTIVE INGREDIENTS: WHITE PETROLATUM; STARCH, CORN; LANOLIN; STEARYL ALCOHOL; BEESWAX; .ALPHA.-BISABOLOL, (+/-)-; CHOLESTEROL; WATER; GLYCERIN; OAT

Triple Paste Adult Care Rash Treatment

Drug Facts

Active ingredient

Zinc oxide 12.8%

Purpose

Skin protectant

Uses

- helps treat and prevent diaper rash
- protects chafed skin due to diaper rash and helps protect from wetness

Warnings

For external use only

When using this productdo not get into eyes.

Stop use and ask a doctor if

- condition worsens
- symptoms last more than 7 days or clear up and occur again within a few days.

Keep out of reach of children.If swallowed, get medical help or contact a Poison Control Center right away.

Directions

- Change wet and soiled undergarments promptly
- Cleanse affected areas and allow skin to dry
- Apply ointment liberally and as often as necessary, with each undergarment change, especially at bedtime or any time when exposure to wetness may be prolonged

Other information

Store at room temperature 15°-30°C (59°-86°F)

Inactive ingredients

white petrolatum, com starch, anhydrous lanolin, stearyl alcohol, beeswax, bisabolol, cholesterol, water, glycerin, oat (avena saliva) kernel extract.

Questions?

1-800-345-0032

Distributed by Advantice Health, LLC
Cedar Knolls, NJ 07927

RECENT MAJOR CHANGES

Update to label copy

PRINCIPAL DISPLAY PANEL - 85 g Tube Carton

TRIPLE PASTE®

Zinc Oxide / Skin Protectant

Adult Care Rash Treatment

•Fragrance-free• Hypoallergenic

PREVENTS

TREATS
SOOTHES

Net Wt. 8oz. (227g)